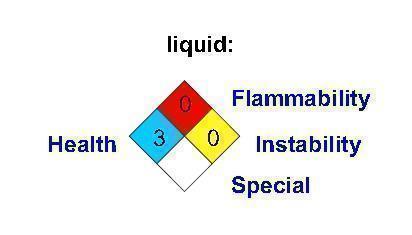 DRUG LABEL: Carbon Dioxide
NDC: 63917-011 | Form: GAS
Manufacturer: Airgas Carbonic, Inc.
Category: animal | Type: PRESCRIPTION ANIMAL DRUG LABEL
Date: 20140512

ACTIVE INGREDIENTS: Carbon Dioxide 1000 mL/1 L

Carbon Dioxide

PACKAGE LABEL

Carbon Dioxide

Liquid: 3 0 0

Health, Flammability, Instability, Special